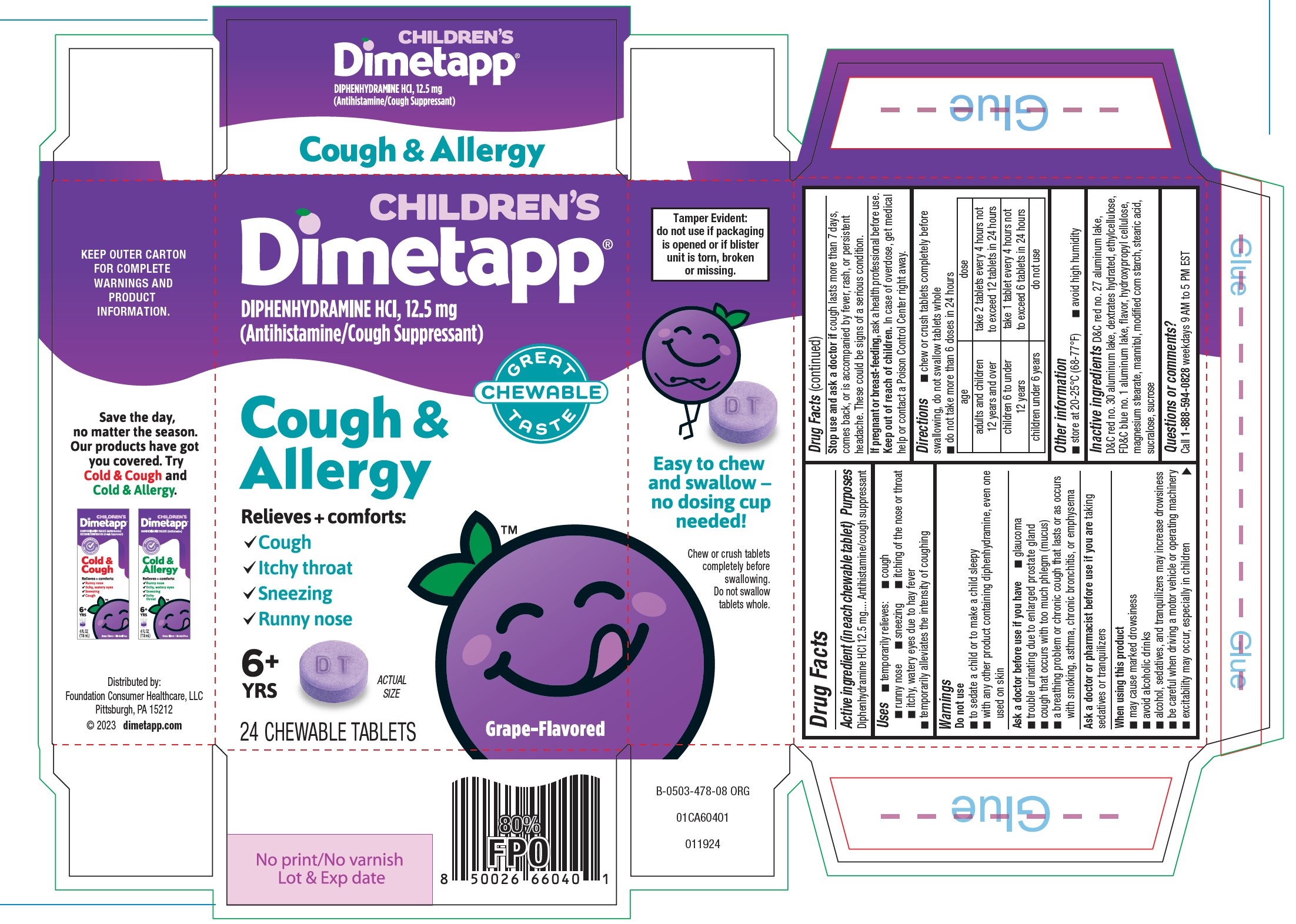 DRUG LABEL: Dimetapp
NDC: 69536-370 | Form: TABLET, CHEWABLE
Manufacturer: Foundation Consumer Healthcare
Category: otc | Type: HUMAN OTC DRUG LABEL
Date: 20240415

ACTIVE INGREDIENTS: DIPHENHYDRAMINE HYDROCHLORIDE 12.5 mg/1 1
INACTIVE INGREDIENTS: FD&C BLUE NO. 1 ALUMINUM LAKE; MODIFIED CORN STARCH (1-OCTENYL SUCCINIC ANHYDRIDE); SUCRALOSE; SUCROSE; D&C RED NO. 30; MAGNESIUM STEARATE; D&C RED NO. 27 ALUMINUM LAKE; DEXTRATES; ETHYLCELLULOSE, UNSPECIFIED; HYDROXYPROPYL CELLULOSE, UNSPECIFIED; MANNITOL; STEARIC ACID

Dimetapp Cough and Allergy Chewable

Drug Facts

ACTIVE INGREDIENT

Diphenhydramine HCl 12.5 mg

PURPOSE

Active ingredients (in each chewable tablet) | Purposes
Diphenhydramine HCl 12.5 mg | Antihistamine/Cough suppresant

Uses

- temporarily relieves:
  - cough
  - runny nose
  - sneezing
  - itching of the nose or throat
  - itchy, watery eyes due to hay fever
- temporarily alleviates the intensity of coughing

Warnings

Do not use

- to sedate a child or make a child sleepy
- with any other product containing diphenhydramine, even one used on skin

Ask a doctor before use if you have

- glaucoma
- trouble urinating due to enlarged prostate gland
- cough that occurs with too much phlegm (mucus)
- a breathing problem or chronic cough that lasts or as occurs with smoking, asthma, chronic bronchitis, or emphysema

Ask a doctor or pharmacist before use if you are

taking sedatives or tranquilizers

When using this product

- may cause marked drowsiness
- avoid alcoholic drinks
- alcohol, sedatives, and tranquilizers may increase drowsiness
- be careful when driving a vehicle or operating machinery
- excitability may occur, expecially in children

Stop use and ask a doctor if

cough lasts more than 7 days, comes back, or is accompanied by fever, rash, or persistent headache. These could be signs of a serious condition.

If pregnant or breast-feeding

ask a health professional before use.

Keep out of reach of children. In case of overdose, get medical help or contact a Poison Control Center right away.

Directions

- chew or crush tablets completely before swallowing, do not swallow tablets whole
- do not take more than 6 doses in 24 hours

age | dose
adults and children 12 years and over | take 2 tablets every 4 hours not to exceed 12 tablets in 24 hours
children 6 to under 12 years | take 1 tablet every 4 hours not to exceed 6 tablets in 24 hours
children under 6 years | do not use

Other information

- store at 20-25°C (68-77°F)
- avoid high humidity

Inactive ingredients

D&C red no.27 aluminum lake, D&C red no.30 aluminum lake, dextrates hydrated, ethylcellulose, FD&C blue no.1 aluminum lake, flavor, hydroxypropyl cellulose, magnesium stearate, mannitol, modified corn starch, stearic acid, sucralose, sucrose

Questions or comments?

Call 1-888-594-0828weekdays 9 AM to 5PM EST

Distributed by:

Foundation Consumer Healthcare, LLC

Pittsburgh, PA 15212

PRINCIPAL DISPLAY PANEL - 24 ct Carton

CHILDREN'S

Dimetapp

DIPHENHYDRAMINE HCl, 12.5 mg

(Antihistamine/Cough Suppressant)

GREAT CHEWABLE TASTE

Cough & Allergy

Relieves + comforts:

- Cough
- Itchy throat
- Sneezing
- Runny nose

6+ years

24 CHEWABLE TABLETS

Grape-Flavored